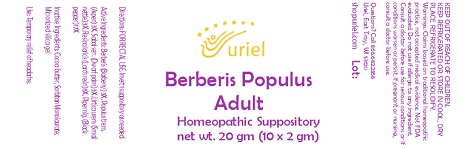 DRUG LABEL: Berberis Populus Adult Size
NDC: 48951-2146 | Form: SUPPOSITORY
Manufacturer: Uriel Pharmacy Inc.
Category: homeopathic | Type: HUMAN OTC DRUG LABEL
Date: 20230929

ACTIVE INGREDIENTS: BERBERIS VULGARIS ROOT BARK 3 [hp_X]/1 g; POPULUS TREMULA WHOLE 3 [hp_X]/1 g; SAW PALMETTO 3 [hp_X]/1 g; URTICA URENS 3 [hp_X]/1 g; LARIX DECIDUA RESIN 8 [hp_X]/1 g; BLACK PEPPER 17 [hp_X]/1 g
INACTIVE INGREDIENTS: COCOA BUTTER; SORBITAN MONOLAURATE; SILICON DIOXIDE

Berberis Populus Adult Size

INDICATIONS AND USAGE

Directions: FOR RECTAL USE.

DOSAGE AND ADMINISTRATION

Insert 1 suppository as needed.

ACTIVE INGREDIENT

Active Ingredients: Berberis (Barberry) 3X, Populus trem. (Aspen) 3X, Sabal serr. (Dwarf palm) 3X, Urtica urens (Small nettle) 3X, Resina laricis (Larch resin) 8X, Piper nig. (Black pepper) 17X

INACTIVE INGREDIENT

Inactive Ingredients: Cocoa butter, Sorbitan Monolaurate, Micronized silica gel

PURPOSE

Use: Temporary relief of headache.

KEEP OUT OF REACH OF CHILDREN.

WARNINGS

KEEP REFRIGERATED OR STORE IN COOL, DRY PLACE. REFRIGERATE TO RESOLIDIFY.
Warnings: Claims based on traditional homeopathic practice, not accepted medical evidence. Not FDA evaluated. Do not use if allergic to any ingredient. Consult a doctor before use for serious conditions or if conditions worsen or persist. If pregnant or nursing, consult a doctor before use. Do not use if safety seals on box are broken or missing.

QUESTIONS

Questions? Call 866.642.2858 Uriel, East Troy, WI 53120 www.urielpharmacy.com